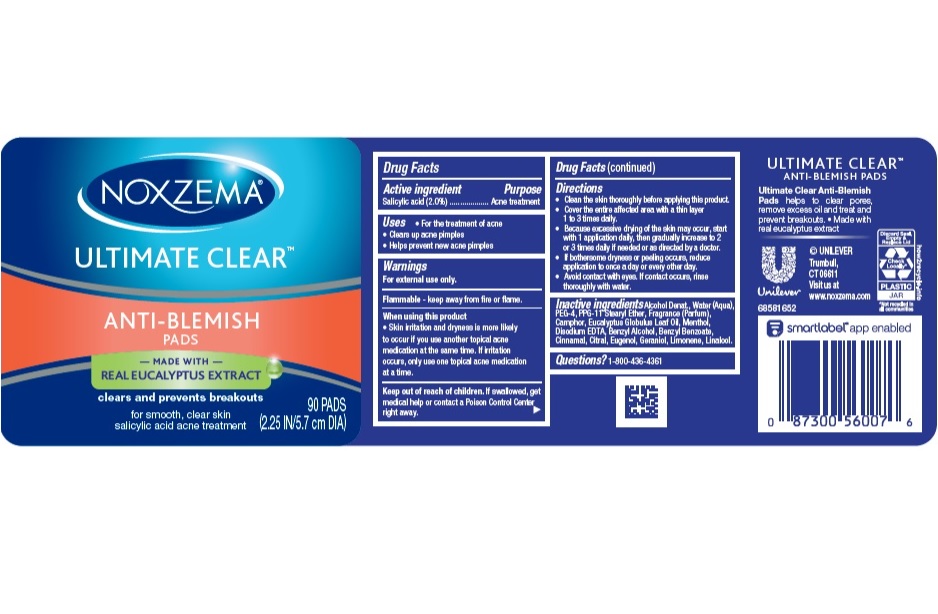 DRUG LABEL: Noxzema
NDC: 64942-1259 | Form: CLOTH
Manufacturer: Conopco Inc.
Category: otc | Type: HUMAN OTC DRUG LABEL
Date: 20241111

ACTIVE INGREDIENTS: SALICYLIC ACID 0.02 g/1 g
INACTIVE INGREDIENTS: ALCOHOL; BENZYL ALCOHOL; CINNAMALDEHYDE; GERANIOL; LIMONENE, (+)-; BENZYL BENZOATE; EUGENOL; LINALOOL, (+/-)-; WATER; POLYETHYLENE GLYCOL 200; PPG-11 STEARYL ETHER; EDETATE DISODIUM; MENTHOL; CAMPHOR (SYNTHETIC); EUCALYPTUS GLOBULUS LEAF; CITRAL

Noxzema Ultimate Clear Anti-Blemish Pads

Drug Facts

Active ingredient

Salicylic Acid (2.0%)

Purpose

Acne treatment

Uses

- For the treatment of acne
- Dries up acne pimples
- Helps prevent new acne pimples

Warnings

- For external use only.
- Flammable - keep away from fire or flame.
- When using this product skin irritation and dryness is more likely to occur if you use another topical acne medication at the same time. If irritation occues, only use one topical acne medication at a time.

- Keep out of reach of children. If swallowed, get medical help or contact a Poison Control Center right away.

Directions

- Clean the skin thoroughly before applying product
- Cover the entire affected area with a thin layer and rinse thoroughly one to three times daily
- Because excessive drying of the skin may occur, start with one application daily, then gradually increase to two or three times daily, if needed or as directed by a doctor.
- If bothersome dryness or peeling occurs, reduce application to once a day or every other day.
- Avoid contact with eyes. If contact occurs, rinse thoroughly with water.

Inactive ingredients

Alcohol Denat., Water (Aqua), PEG-4, PPG-11 Stearyl Ether, Fragrance (Parfum), Camphor, Eucalyptus Globulus Leaf Oil, Menthol, Disodium EDTA, Benzyl Alcohol, Benzyl Benzoate, Cinnamal, Citral, Eugenol, Geraniol, Geraniol, Limonene, Linalool.

Questions?

1-800-436-4361